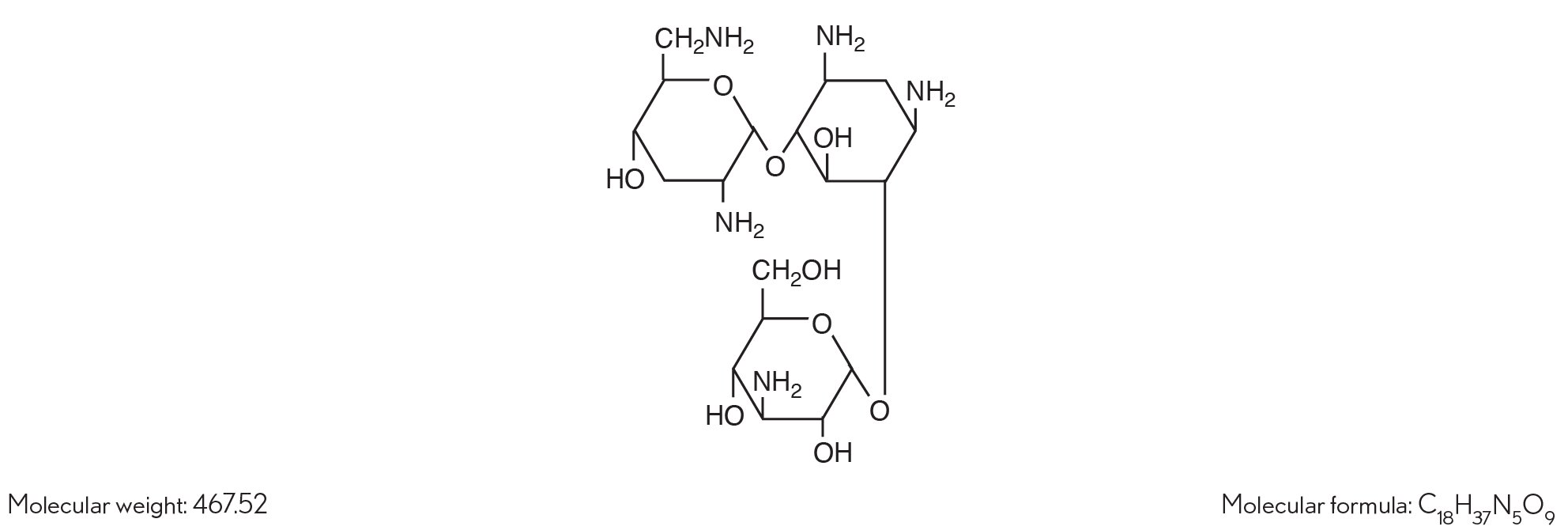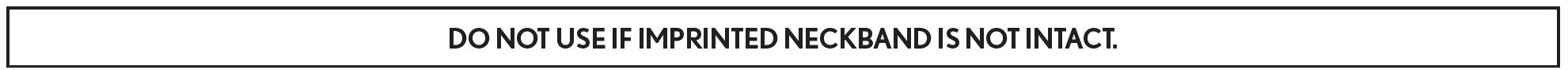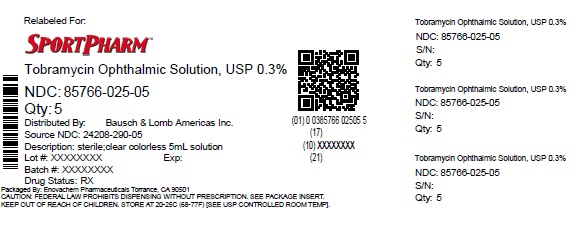 DRUG LABEL: Tobramycin
NDC: 85766-025 | Form: SOLUTION
Manufacturer: Sportpharm LLC
Category: prescription | Type: HUMAN PRESCRIPTION DRUG LABEL
Date: 20260205

ACTIVE INGREDIENTS: TOBRAMYCIN 3 mg/1 mL
INACTIVE INGREDIENTS: BORIC ACID; WATER; SODIUM CHLORIDE; SODIUM HYDROXIDE; SODIUM SULFATE; SULFURIC ACID; TYLOXAPOL

Tobramycin
Ophthalmic Solution, USP
0.3%
(Sterile)
Rx only

DESCRIPTION

Tobramycin ophthalmic solution USP, 0.3% is a sterile topical ophthalmic antibiotic formulation prepared specifically for topical therapy of external ophthalmic infections.

Each mL contains:

Active:tobramycin 3 mg (0.3%). Inactives:boric acid, sodium sulfate, sodium chloride, tyloxapol and purified water. Sodium hydroxide and/or sulfuric acid (to adjust pH). Tobramycin ophthalmic solution, 0.3% has a pH range between 7.0 and 8.0.

Preservative:benzalkonium chloride 0.1 mg (0.01%).

Tobramycin is a water-soluble aminoglycoside antibiotic active against a wide variety of gram-negative and gram-positive ophthalmic pathogens.

The chemical structure of tobramycin is:

Chemical name:

(2S,3R,4S,5S,6R)-4-amino-2-[(1S,2S,3R,4S,6R)-4,6-diamino-3-[(2R,3R,5S,6R)-3-amino-6-(aminomethyl)-5-hydroxyoxan-2-yl]oxy-2-hydroxycyclohexyl]oxy-6-(hydroxymethyl)oxane-3,5-diol

CLINICAL PHARMACOLOGY

In Vitro Data: In vitrostudies have demonstrated tobramycin is active against susceptible strains of the following microorganisms: Staphylococci, including S. aureusand S. epidermidis(coagulase-positive and coagulase-negative), including penicillin-resistant strains.

Streptococci, including some of the Group A-beta-hemolytic species, some nonhemolytic species, and some Streptococcus pneumoniae.

Pseudomonas aeruginosa, Escherichia coli, Klebsiella pneumoniae, Enterobacter aerogenes, Proteus mirabilis, Morganella morganii,most Proteus vulgarisstrains, Haemophilus influenzaeand H. aegyptius, Moraxella lacunata, Acinetobacter calcoaceticusand some Neisseriaspecies. Bacterial susceptibility studies demonstrate that in some cases, microorganisms resistant to gentamicin retain susceptibility to tobramycin.

INDICATIONS AND USAGE

Tobramycin ophthalmic solution, 0.3% is a topical antibiotic indicated in the treatment of external infections of the eye and its adnexa caused by susceptible bacteria. Appropriate monitoring of bacterial response to topical antibiotic therapy should accompany the use of tobramycin ophthalmic solution. Clinical studies have shown tobramycin to be safe and effective for use in children.

CONTRAINDICATIONS

Tobramycin ophthalmic solution, 0.3% is contraindicated in patients with known hypersensitivity to any of its components.

WARNINGS

FOR TOPICAL OPHTHALMIC USE ONLY. NOT FOR INJECTION INTO THE EYE.

Sensitivity to topically applied aminoglycosides may occur in some patients. Severity of hypersensitivity reactions may vary from local effects to generalized reactions such as erythema, itching, urticaria, skin rash, anaphylaxis, anaphylactoid reactions, or bullous reactions. If a sensitivity reaction to tobramycin ophthalmic solution, 0.3% occurs, discontinue use.

PRECAUTIONS

General

As with other antibiotic preparations, prolonged use may result in overgrowth of nonsusceptible organisms, including fungi. If superinfection occurs, appropriate therapy should be initiated.

Cross-sensitivity to other aminoglycoside antibiotics may occur; if hypersensitivity develops with this product, discontinue use and institute appropriate therapy. Patients should be advised not to wear contact lenses if they have signs and symptoms of bacterial ocular infection.

Information for Patients

Do not touch dropper tip to any surface, as this may contaminate the solution.

Pregnancy

Reproduction studies in 3 types of animals at doses up to 33 times the normal human systemic dose have revealed no evidence of impaired fertility or harm to the fetus due to tobramycin. There are, however, no adequate and well-controlled studies in pregnant women. Because animal studies are not always predictive of human response, this drug should be used during pregnancy only if clearly needed.

Nursing Mothers

Because of the potential for adverse reactions in nursing infants from tobramycin ophthalmic solution, a decision should be made whether to discontinue nursing the infant or discontinue the drug, taking into account the importance of the drug to the mother.

Pediatric Use

Safety and effectiveness in pediatric patients below the age of 2 months has not been established.

Geriatric Use

No overall differences in safety or effectiveness have been observed between elderly and younger patients.

ADVERSE REACTIONS

The most frequent adverse reactions to tobramycin ophthalmic solution, 0.3% are hypersensitivity and localized ocular toxicity, including lid itching and swelling, and conjunctival erythema. These reactions occur in less than three of 100 patients treated with tobramycin ophthalmic solution.

Postmarketing Experience

Additional adverse reactions identified from postmarketing use include anaphylactic reaction, Stevens-Johnson syndrome, and erythema multiforme.

The following additional adverse reactions have been reported with systemic aminoglycosides:

Neurotoxicity, ototoxicity and nephrotoxicity have occurred in patients receiving systemic aminoglycoside therapy. Aminoglycosides may aggravate muscle weakness in patients with known or suspected neuromuscular disorders, such as myasthenia gravis or Parkinson’s disease, because of their potential effect on neuromuscular function.

To report SUSPECTED ADVERSE REACTIONS, contact Bausch & Lomb Incorporated at 1-800-553-5340 or FDA at 1-800-FDA-1088 or www.fda.gov/medwatch.

DOSAGE AND ADMINISTRATION

In mild to moderate disease, instill 1 or 2 drops into the affected eye(s) every 4 hours. In severe infections, instill 2 drops into the eye(s) hourly until improvement, following which treatment should be reduced prior to discontinuation.

FOR TOPICAL OPHTHALMIC USE ONLY

HOW SUPPLIED

Tobramycin ophthalmic solution USP, 0.3% is supplied in a plastic bottle with a controlled drop tip and a white polypropylene cap in the following size:

NDC 85766-025-05 - 5 mL fill in a 10 mL bottle (relabeled from NDC 24208-290-05)

Storage

Store at 2°C to 25°C (36°F to 77°F). Avoid excessive heat.

After opening, tobramycin ophthalmic solution USP, 0.3% can be used until the expiration date on the bottle.

Distributed by:

Sportpharm LLC
379 Van Ness Ave 1401,
Torrance, CA 90501

Relabeled by:

Enovachem PHARMACEUTICALS

Torrance, CA 90501